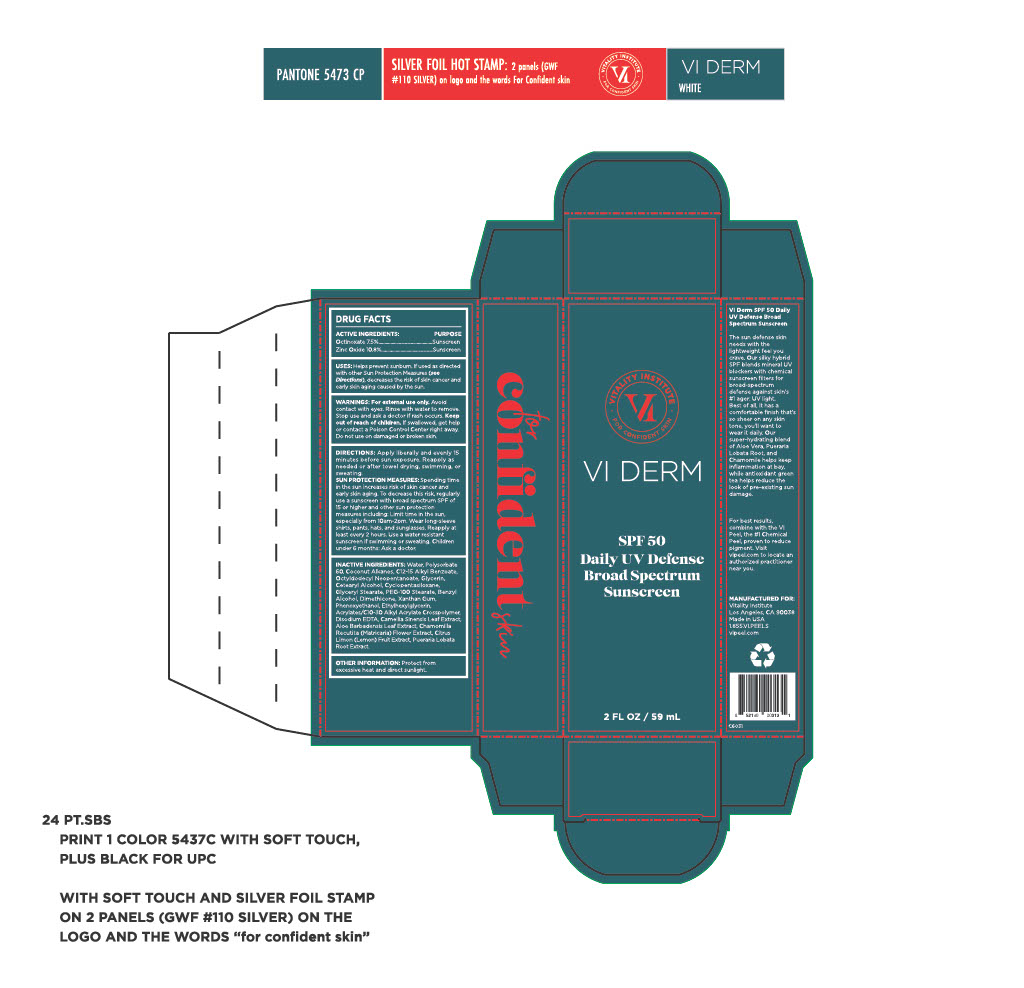 DRUG LABEL: SPF 50 Daily UV Defense Broad Spectrum Sunscreen
NDC: 70484-008 | Form: CREAM
Manufacturer: Vi Medical Products, INC
Category: otc | Type: HUMAN OTC DRUG LABEL
Date: 20250619

ACTIVE INGREDIENTS: ZINC OXIDE 10.8 g/100 mL; OCTINOXATE 7.5 g/100 mL
INACTIVE INGREDIENTS: CYCLOPENTASILOXANE; BENZYL ALCOHOL; XANTHAN GUM; PUERARIA MONTANA VAR. LOBATA ROOT; ACRYLATES/C10-30 ALKYL ACRYLATE CROSSPOLYMER (60000 MPA.S); CETEARYL ALCOHOL; MATRICARIA RECUTITA FLOWERING TOP; ALOE VERA LEAF; PEG-100 STEARATE; GLYCERYL STEARATE; ETHYLHEXYLGLYCERIN; LEMON; GLYCERIN; POLYSORBATE 60; PHENOXYETHANOL; C12-15 ALKYL BENZOATE; EDETATE DISODIUM; GREEN TEA LEAF; OCTYLDODECYL NEOPENTANOATE; DIMETHICONE; WATER; COCONUT ALKANES

SPF 50 Daily UV Defense Broad Spectrum Sunscreen

Active ingredients purpose

Octinoxate 7.5% Sunscreen

Zinc Oxide 10.8 Sunscreen

PURPOSE

Uses: Helps prevent sunburn if used as directed with other sun protection (see directions), decreases the risk of skin cancer and early skin aging caused by the sun.

Keep out of reach of children. If swallowed, get help or contact a Poison Control Center right away.

Stop use and ask a doctor if rash occurs

Warnings:

For external use only. Avoid contact with eyes. Rinse with water to remove. Do not use on damaged or broken skin.

DOSAGE AND ADMINISTRATION

Directions: Apply liberally and evenly 15 minutes before sun exposure. Reapply as needed or after towel drying, swimming, or sweating.

Sun Protection Measures: Spending time in the sun increases risk of skin cancer and early skin aging. To decrease this risk, regularly use a sunscreen with a broad spectrum SPF of 15 or higher and other sun protection measures including:

Limit time in the sun, especially from 10am-2pm. Wear long-sleeved shirts, pants, hats and sunglasses

Reapply at least 2 hours. Use a water resistant sunscreen if swimming or sweating.

Children under 6 months, ask a doctor.

INACTIVE INGREDIENT

Inactive ingredients: Water, Polysorbate 60, Coconut Alkanes, C12-15 Alkyl Benzoate, Octyldodecanol Neopentanoate, Glycerin, Cetearyl Alcohol, Cyclopentasiloxane, Glyceryl Stearate, PEG-100 Stearate, Benzyl Alcohol, Dimeticone, Xanthan Gum, Phenoxyethanol, Ethylhexylgycerin, Acrylates/C10-30 Alkyl Acrylate Crosspolymer, Disodium EDTA, Camellia Sinensis Leaf Extract, Aloe Barbadensis Leaf Extract, Chamomilla Recutita (Matricaria) Flower Extract, Citrus Limon (Lemon) Fruit Extract, Pueraria Lobata Root Extract

PACKAGE LABEL

Vitality Institute

SPF 50 Daily UV Defense Broad Spectrum Sunscreen

2 Fl Oz / 59 mL